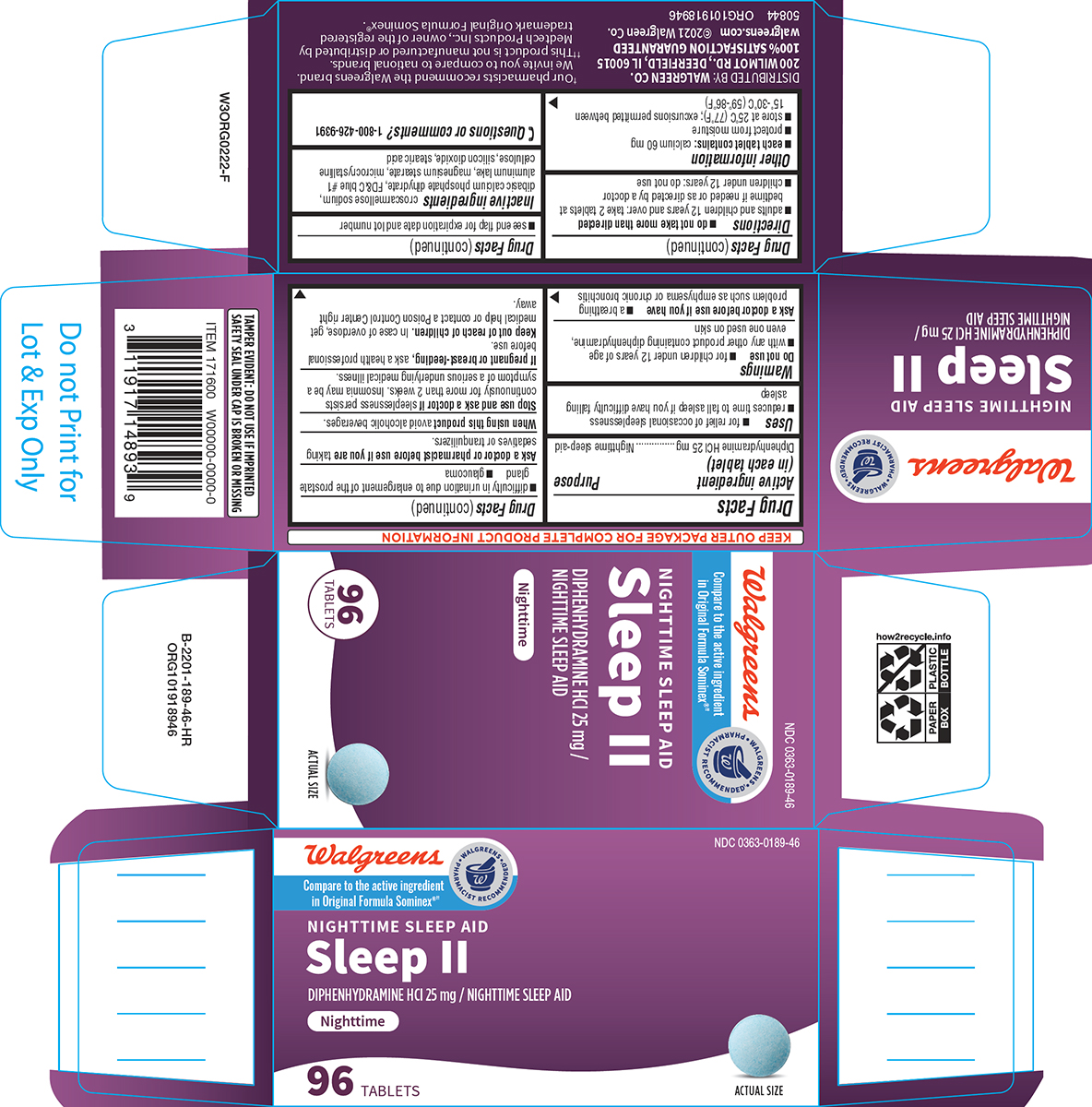 DRUG LABEL: Sleep II
NDC: 0363-0189 | Form: TABLET
Manufacturer: Walgreen Company
Category: otc | Type: HUMAN OTC DRUG LABEL
Date: 20250510

ACTIVE INGREDIENTS: DIPHENHYDRAMINE HYDROCHLORIDE 25 mg/1 1
INACTIVE INGREDIENTS: CROSCARMELLOSE SODIUM; DIBASIC CALCIUM PHOSPHATE DIHYDRATE; FD&C BLUE NO. 1 ALUMINUM LAKE; MAGNESIUM STEARATE; MICROCRYSTALLINE CELLULOSE; SILICON DIOXIDE; STEARIC ACID

Walgreens 44-189

Active ingredient (in each tablet)

Diphenhydramine HCl 25 mg

Purpose

Nighttime sleep-aid

Uses

- for relief of occasional sleeplessness
- reduces time to fall asleep if you have difficulty falling asleep

Warnings

Do not use

- for children under 12 years of age
- with any other product containing diphenhydramine, even one used on skin

Ask a doctor before use if you have

- a breathing problem such as emphysema or chronic bronchitis
- difficulty in urination due to enlargement of the prostate gland
- glaucoma

Ask a doctor or pharmacist before use if you are

taking sedatives or tranquilizers.

When using this product

avoid alcoholic beverages.

Stop use and ask a doctor if

sleeplessness persists continuously for more than 2 weeks. Insomnia may be a symptom of a serious underlying medical illness.

If pregnant or breast-feeding,

ask a health professional before use.

Keep out of reach of children.

In case of overdose, get medical help or contact a Poison Control Center right away.

Directions

- do not take more than directed
- adults and children 12 years and over: take 2 tablets at bedtime if needed or as directed by a doctor
- children under 12 years: do not use

Other information

- each tablet contains: calcium 60 mg
- protect from moisture
- store at 25°C (77°F); excursions permitted between 15°-30°C (59°-86°F)
- see end flap for expiration date and lot number

Inactive ingredients

croscarmellose sodium, dibasic calcium phosphate dihydrate, FD&C blue #1 aluminum lake, magnesium stearate, microcrystalline cellulose, silicon dioxide, stearic acid

Questions or comments?

1-800-426-9391

Principal Display Panel

Walgreens

WALGREENS PHARMACIST RECOMMENDED†

Compare to the active ingredient
in Original Formula Sominex®††

NDC 0363-0189-46

NIGHTTIME SLEEP AID
Sleep II
DIPHENHYDRAMINE HCl 25 mg /
NIGHTTIME SLEEP AID

Nighttime

96 TABLETS

ACTUAL SIZE

TAMPER EVIDENT: DO NOT USE IF IMPRINTED
SAFETY SEAL UNDER CAP IS BROKEN OR MISSING

DISTRIBUTED BY: WALGREEN CO.
200 WILMOT RD., DEERFIELD, IL 60015
100% SATISFACTION GUARANTEED
walgreens.com ©2021 Walgreen Co.

50844 ORG101918946

†Our pharmacists recommend the Walgreens brand.
We invite you to compare to national brands.
††This product is not manufactured or distributed by
Medtech Products Inc., owner of the registered
trademark Original Formula Sominex®.

Walgreens 44-189